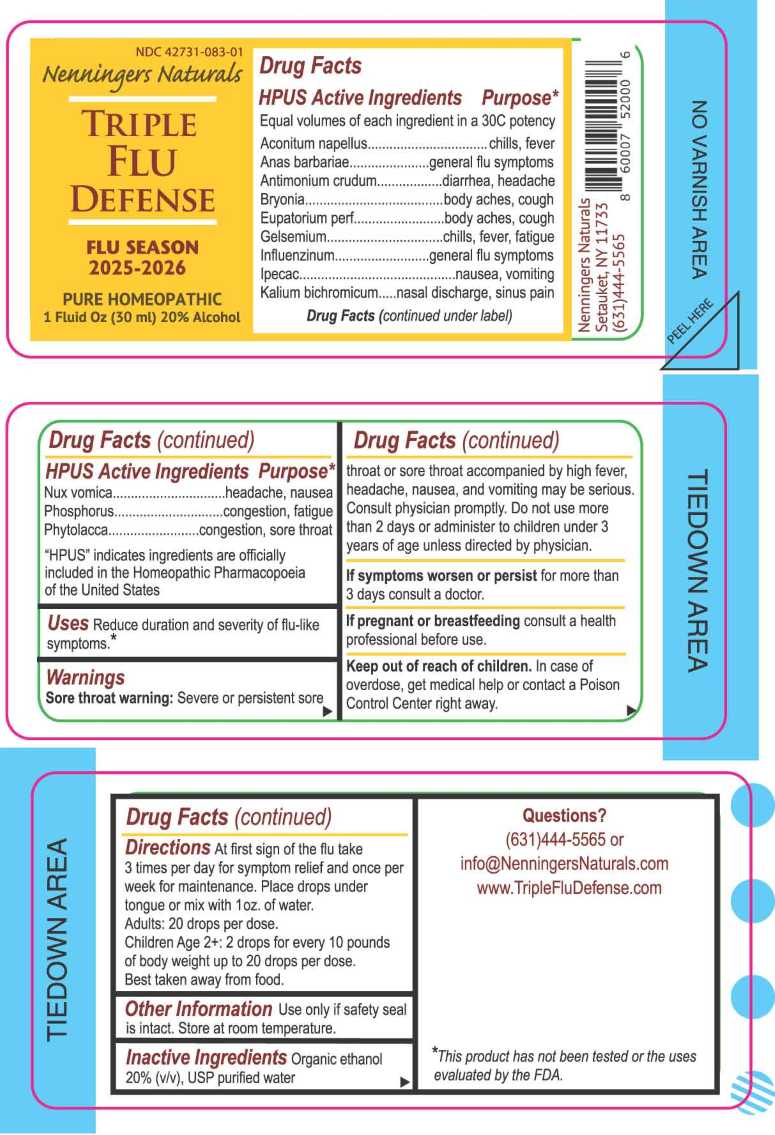 DRUG LABEL: Triple Flu Defense
NDC: 42731-083 | Form: LIQUID
Manufacturer: Nenningers Naturals, LLC
Category: homeopathic | Type: HUMAN OTC DRUG LABEL
Date: 20251125

ACTIVE INGREDIENTS: ACONITUM NAPELLUS WHOLE 30 [hp_C]/1 mL; CAIRINA MOSCHATA HEART/LIVER AUTOLYSATE 30 [hp_C]/1 mL; ANTIMONY TRISULFIDE 30 [hp_C]/1 mL; BRYONIA ALBA ROOT 30 [hp_C]/1 mL; EUPATORIUM PERFOLIATUM FLOWERING TOP 30 [hp_C]/1 mL; GELSEMIUM SEMPERVIRENS ROOT 30 [hp_C]/1 mL; INFLUENZA A VIRUS A/VICTORIA/4897/2022 IVR-238 (H1N1) ANTIGEN (FORMALDEHYDE INACTIVATED) 30 [hp_C]/1 mL; INFLUENZA A VIRUS A/THAILAND/8/2022 IVR-237 (H3N2) ANTIGEN (FORMALDEHYDE INACTIVATED) 30 [hp_C]/1 mL; INFLUENZA B VIRUS B/AUSTRIA/1359417/2021 BVR-26 WHOLE 30 [hp_C]/1 mL; INFLUENZA B VIRUS B/PHUKET/3073/2013 BVR-1B WHOLE 30 [hp_C]/1 mL; IPECAC 30 [hp_C]/1 mL; POTASSIUM DICHROMATE 30 [hp_C]/1 mL; STRYCHNOS NUX-VOMICA SEED 30 [hp_C]/1 mL; PHOSPHORUS 30 [hp_C]/1 mL; PHYTOLACCA AMERICANA ROOT 30 [hp_C]/1 mL
INACTIVE INGREDIENTS: WATER; ALCOHOL

DRUG FACTS:

ACTIVE INGREDIENTS:

Aconitum Napellus 30C, Anas Barbariae, Hepatis ET Cordis Extractum 30C, Antimonium Crudum 30C, Bryonia 30C, Eupatorium Perfoliatum 30C, Gelsemium Sempervirens 30C, Influenzinum 30C, Ipecacuanha 30C, Kali Bichromicum 30C, Nux Vomica 30C, Phosphorus 30C, Phytolacca Decandra 30C.

"HPUS" indicates ingredients are officially included in the Homeopathic Pharmacopoeia of the United States.

PURPOSE:

Aconitum Napellus – chills, fever,* Anas Barbariae - general flu symptoms,* Antimonium Crudum – diarrhea, headache,* Bryonia – body aches, cough,* Eupatorium Perfoliatum – body aches, cough,* Gelsemium Sempervirens – chills, fever, fatigue,* Influenzinum – general flu symptoms,* Ipecacuanha – nausea, vomiting,* Kali Bichromicum – nasal discharge, sinus pain,* Nux Vomica – headache, nausea,* Phosphorus – congestion, fatigue,* Phytolacca Decandra – congestion, sore throat*

*This product has not been tested or the uses evaluated by the FDA.

USES:

Reduce duration and severity of flu-like symptoms.*

*This product has not been tested or the uses evaluated by the FDA.

WARNINGS:

Sore Throat Warning: Severe or persistent sore throat or sore throat accompanied by high fever, headache, nausea, and vomiting may be serious. Consult physician promptly. Do not use more than 2 days or administer to children under 3 years of age unless directed by a physician.

If symptoms worsen or persist for more than 3 days consult a doctor.

If pregnant or breast-feeding, consult a health professional before use.

Keep out of reach of children. In case of overdose, get medical help or contact a Poison Control Center right away.

Use only if safety seal is intact.

Store at room temperature.

KEEP OUT OF REACH OF CHILDREN:

In case of overdose, get medical help or contact a Poison Control Center right away.

DIRECTIONS:

At first sign of the flu take 3 times per day for symptom relief and once per week for maintenance. Place drops under tongue or mix with 1oz of water.

Adults: 20 drops per dose.

Children Age 2+: 2 drops for every 10 pounds of body weight up to 20 drops per dose.

Best taken away from food.

INACTIVE INGREDIENTS:

20% (v/v), USP purified water

QUESTIONS:

Nenningers Naturals

Setauket, NY 11733

(631)444-5565

info@NenningersNaturals.com

www.TripleFluDefense.com

PACKAGE LABEL DISPLAY:

NDC 42731-083-01

Nenningers Naturals

TRIPLE FLU

DEFENSE

PURE HOMEOPATHIC

1 Fluid Oz (30mL)